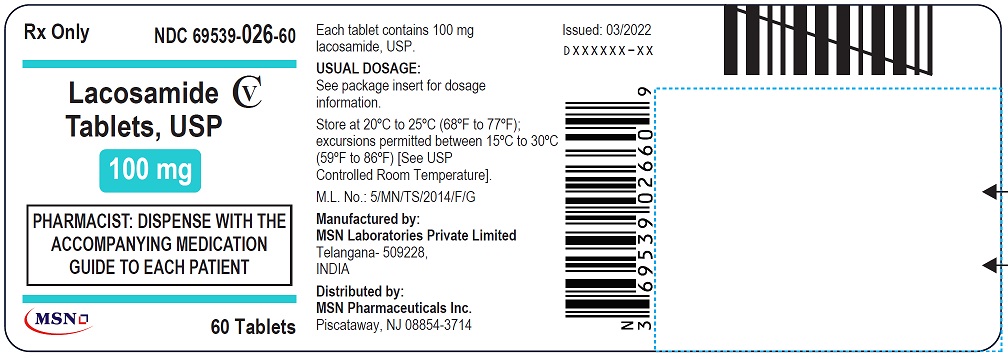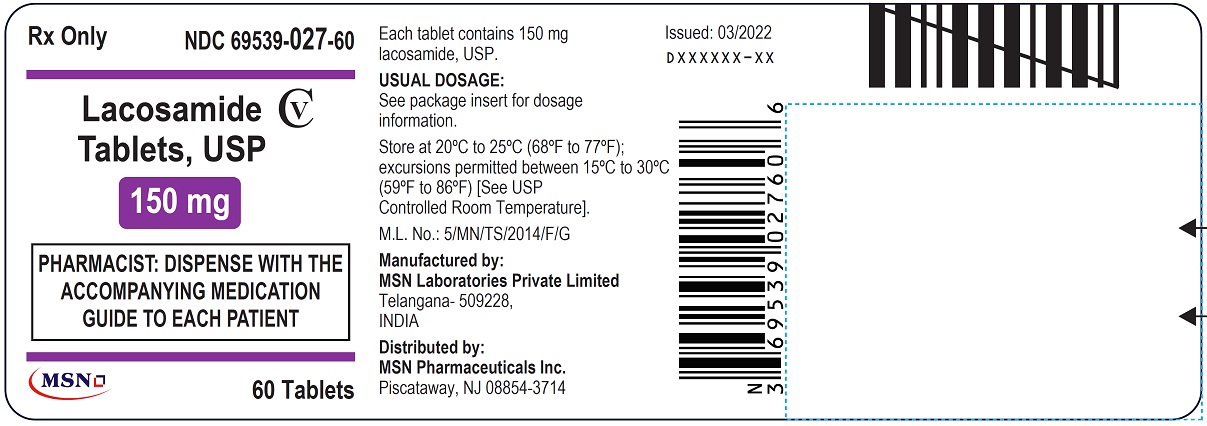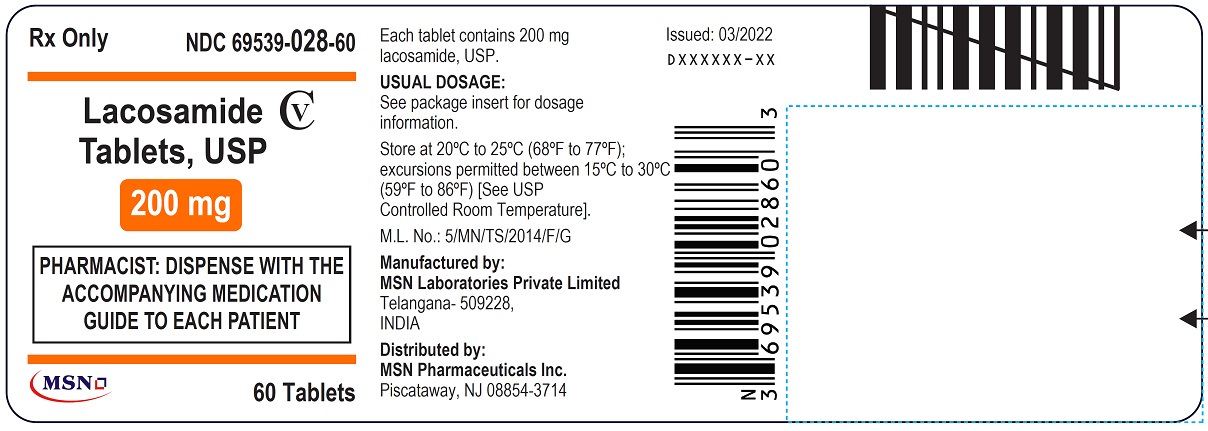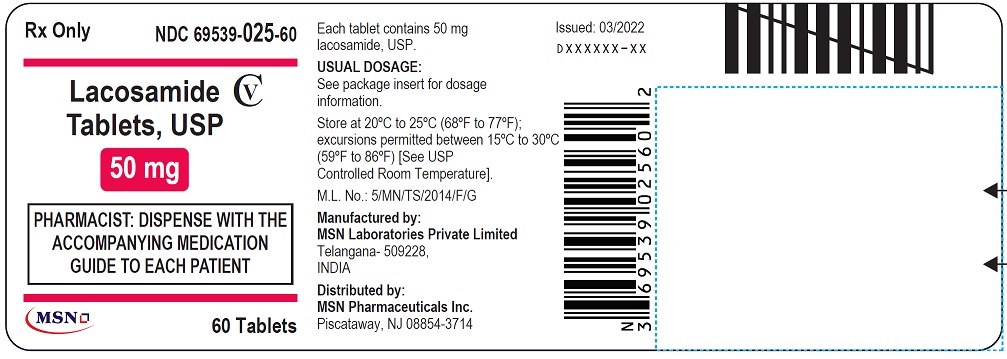 DRUG LABEL: lacosamide
NDC: 69539-025 | Form: TABLET, FILM COATED
Manufacturer: MSN LABORATORIES  PRIVATE LIMITED
Category: prescription | Type: Human Prescription Drug Label
Date: 20220421
DEA Schedule: CV

ACTIVE INGREDIENTS: LACOSAMIDE 50 mg/1 1
INACTIVE INGREDIENTS: CROSPOVIDONE (120 .MU.M); LOW-SUBSTITUTED HYDROXYPROPYL CELLULOSE, UNSPECIFIED; MICROCRYSTALLINE CELLULOSE; FD&C BLUE NO. 2; FERRIC OXIDE RED; FERROSOFERRIC OXIDE; HYDROXYPROPYL CELLULOSE (1600000 WAMW); LECITHIN, SOYBEAN; MAGNESIUM STEARATE; POLYETHYLENE GLYCOL, UNSPECIFIED; POLYVINYL ALCOHOL, UNSPECIFIED; SILICON DIOXIDE; TALC; TITANIUM DIOXIDE

LACOSAMIDE film coated tablet, for oral use, CV

PACKAGE LABEL.PRINCIPAL DISPLAY PANEL

NDC 69539-025-60

Lacosamide Tablet, USP

50 mg

Rx Only

PHARMACIST: DISPENSE WITH THE ACCOMPANYING MEDICATION GUIDE TO EACH PATIENT

60 Tablets

NDC 69539-026-60

Lacosamide Tablet, USP

100 mg

Rx Only

PHARMACIST: DISPENSE WITH THE ACCOMPANYING MEDICATION GUIDE TO EACH PATIENT

60 Tablets

NDC 69539-027-60

Lacosamide Tablet, USP

150 mg

Rx Only

PHARMACIST: DISPENSE WITH THE ACCOMPANYING MEDICATION GUIDE TO EACH PATIENT

60 Tablets

NDC 69539-028-60

Lacosamide Tablet, USP

200 mg

Rx Only

PHARMACIST: DISPENSE WITH THE ACCOMPANYING MEDICATION GUIDE TO EACH PATIENT

60 Tablets